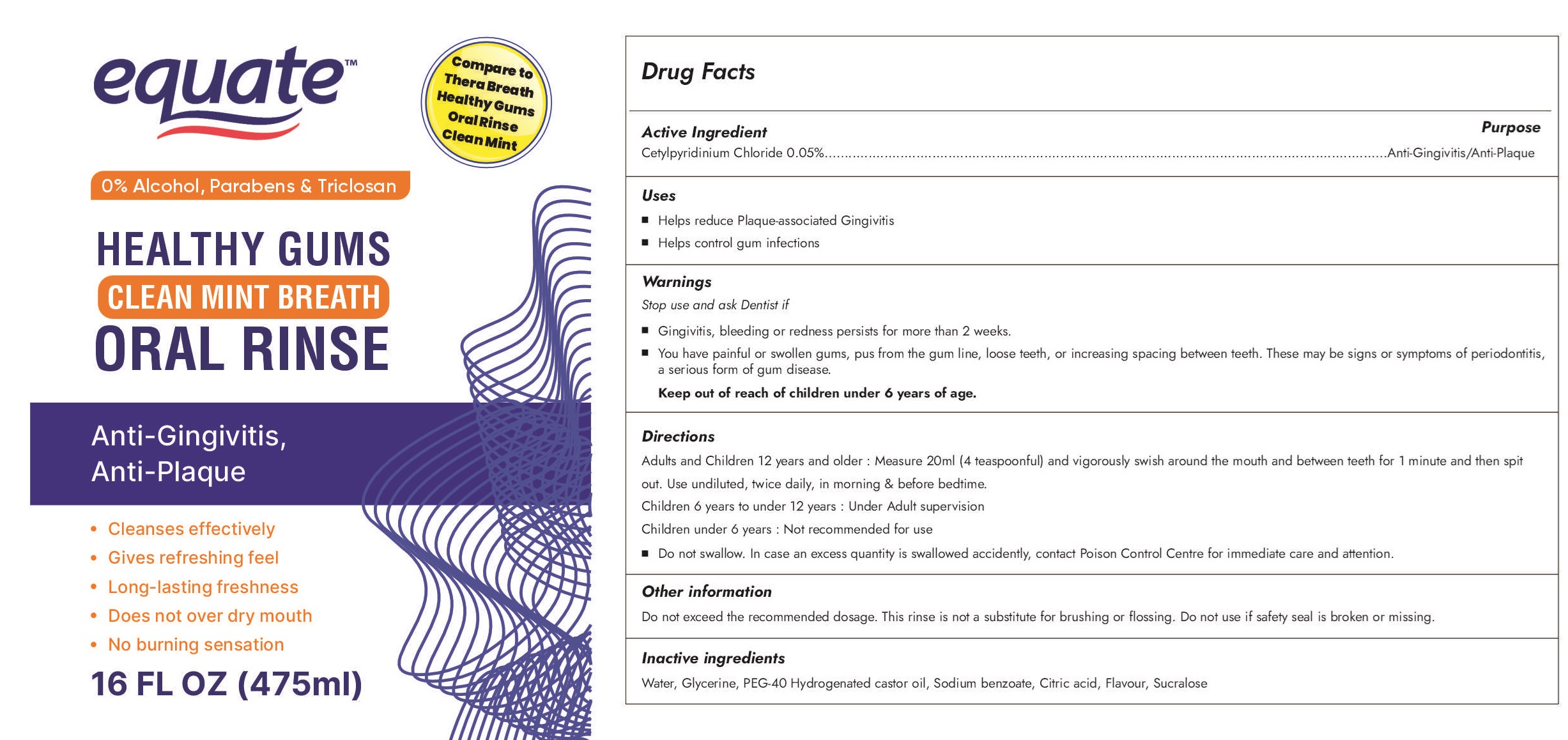 DRUG LABEL: Equate Healthy Gums Clean Mint Breath Oral Rinse
NDC: 84239-000 | Form: LIQUID
Manufacturer: Vasu Healthcare Pvt. Ltd.
Category: otc | Type: HUMAN OTC DRUG LABEL
Date: 20241211

ACTIVE INGREDIENTS: CETYLPYRIDINIUM CHLORIDE 0.5 mg/1 mL
INACTIVE INGREDIENTS: WATER; GLYCERIN; POLYOXYL 40 HYDROGENATED CASTOR OIL; SODIUM BENZOATE; CITRIC ACID MONOHYDRATE; SUCRALOSE

Equate Healthy Gums Clean Mint Breath Oral Rinse

Active Ingredient

Cetylpyridinium Chloride 0.05%

Purpose

Anti-Gingivitis/Anti-Plaque

Uses

- Helps reduce Plaque-associated Gingivitis
- Helps control gum infections

Warnings

Stop use and ask Dentist if

- Gingivitis, bleeding or redness persists for more than 2 weeks.
- You have painful or swollen gums, pus from the gum line, loose teeth, or increasing spacing between teeth. These may be signs or symptoms of periodontitis, a serious form of gum disease.

Keep out of reach of children

under 6 years of age.

Directions

Adults and children 12 years and older : Measure 20ml (4 teaspoonful) and vigorously swish around the mouth and between teeth for 1 minute then spit out. Use undiluted, twice daily, in morning & before bedtime.

Children 6 years to under 12 years : Under Adult supervision

Children under 6 years : Not recommended for use

- Do not swallow. In case as excess quantity is swallowed accidently, contact Poison Control Center for immediate care and attention.

Other information

Do not exceed the recommended dosage. This rinse is not a substitute for brushing or flossing. Do not use if safety seal is broken or missing.

Inactive ingredients

Water, Glycerin, PEG-40 Hydrogenated castor oil, Sodium benzoate, Citric acid, Flavour, Sucralose